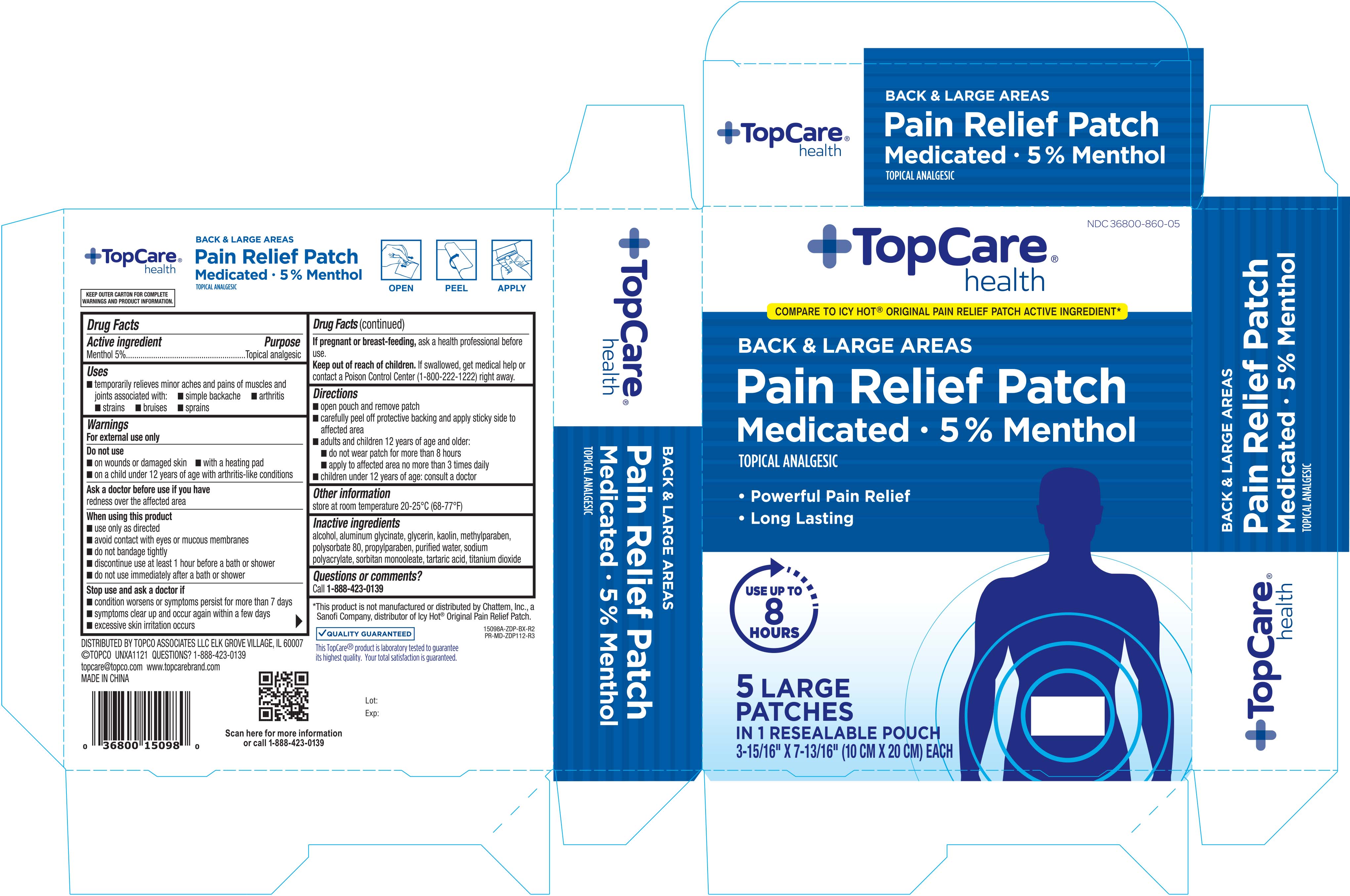 DRUG LABEL: Topcare Cold and Hot Medicated
NDC: 36800-860 | Form: PATCH
Manufacturer: Topco Associates LLC
Category: otc | Type: HUMAN OTC DRUG LABEL
Date: 20251031

ACTIVE INGREDIENTS: MENTHOL 50 mg/1 1
INACTIVE INGREDIENTS: METHYLPARABEN; TITANIUM DIOXIDE; PROPYLPARABEN; ALCOHOL; KAOLIN; TARTARIC ACID; DIHYDROXYALUMINUM AMINOACETATE ANHYDROUS; POLYSORBATE 80; WATER; SODIUM POLYACRYLATE (8000 MW); SORBITAN MONOOLEATE

Topcare Cold & Holt Medicated Patch 5 ct. Large 15098A

Active ingredient Purpose

Menthol 5%..................................................Topical analgesic

Uses

- temporarily relieves minor aches and pains of muscles and joints associated with:
- simple backache
- arthritis
- strains
- bruises
- sprains

Warnings

For external use only

Do not use

- on wounds or damaged skin
- with a heating pad
- on a child under 12 years of age with arthritis-like-conditions

Ask a doctor before use if you have

redness over the affected area

When using this product

- use only as directed
- avoid contact with eyes or mucous membranes
- do not bandage tightly
- discontinue use at least 1 hour before a bath or shower
- do not use immediately after a bath or shower

Stop use and ask a doctor if

- condition worsens or symptoms persist for more than 7 days
- symptoms clear up and occur again within a few days
- excessive skin irritation occurs

PREGNANCY OR BREAST FEEDING

If pregnant or breast-feeding, ask a health professional before use.

Keep out of reach of children. If swallowed, get medical help or contact a Poison Control Center (1-800-222-1222) right away

Directions

- open pouch and remove patch
- carefully peel off protective backing and apply sticky side to affected area
- adults and children 12 years of age and older:
- do not wear patch for more than 8 hours
- apply to affected area no more than 3 times daily
- children under 12 years of age: consult a doctor

Other information

- store at room temperature 20-25°C (68-77°F)

Inactive ingredients

alcohol, aluminum glycinate, glycerin, kaolin, methylparaben, polysorbate 80, propylparaben, purified water, sodium polyacrylate, sorbitan monooleate, tartaric acid, titanium dioxide

DOSAGE AND ADMINISTRATION

Distributed by:

Topco Associates LLC

Elk Grove Village, IL 60007

Made in China